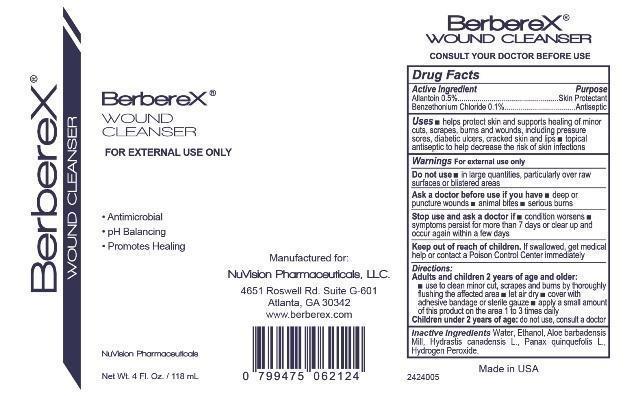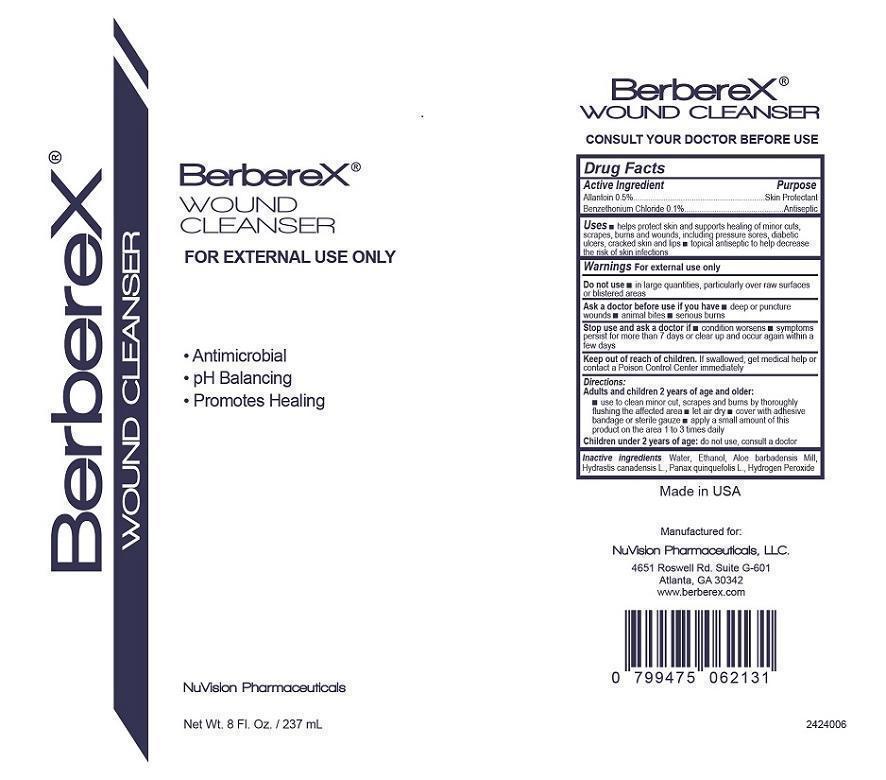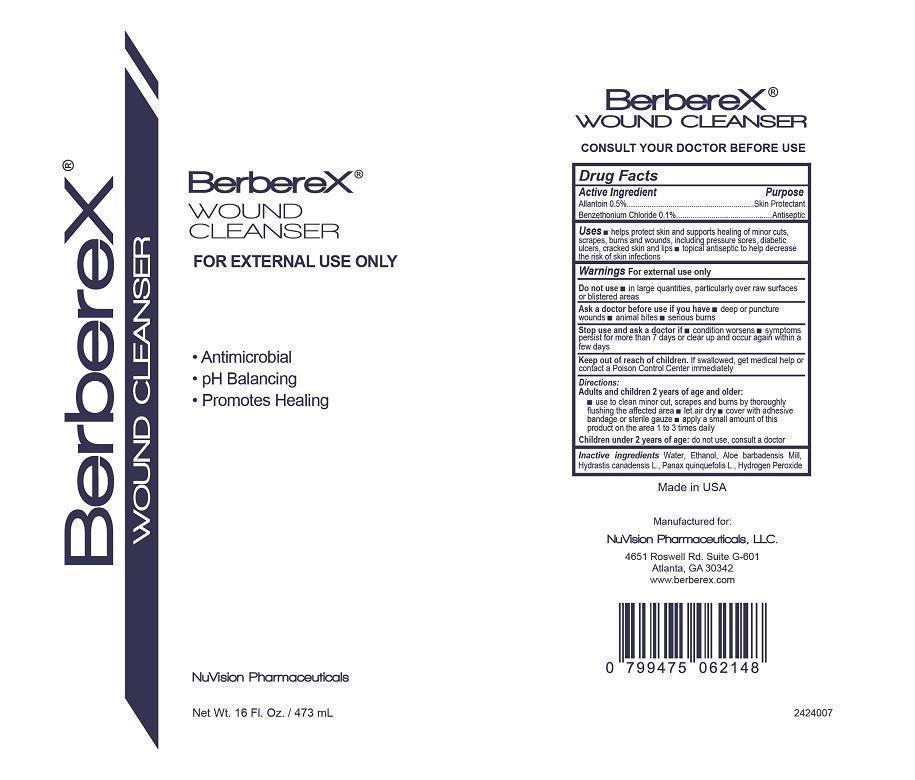 DRUG LABEL: BerbereX Wound Cleanser
NDC: 52261-0500 | Form: LIQUID
Manufacturer: Cosco International, Inc.
Category: otc | Type: HUMAN OTC DRUG LABEL
Date: 20250530

ACTIVE INGREDIENTS: ALLANTOIN 5 g/1000 mL; BENZETHONIUM CHLORIDE 1 g/1000 mL
INACTIVE INGREDIENTS: water; ALCOHOL; ALOE VERA WHOLE; HYDRASTIS CANADENSIS WHOLE; PANAX QUINQUEFOLIUS WHOLE; hydrogen peroxide

Drug Facts

Active Ingredient/Purpose

Allantoin 0.5%........................Skin Protectant

Benzethonium Chloride 0.1%............Antiseptic

Uses

- helps protect skin and supports healing of minor cuts, scrapes, burns and wounds, including pressure sores, diabetic ulcers, cracked skin and lips
- topical antiseptic to help decrease the risk of skin infections

Warnings For external use only.

Do not use

- in large quantities, particularly over raw surfaces or blistered areas

Ask doctor before use if you have

- deep or puncture wounds
- animal bites
- serious burns

Stop use and ask doctor if

- condition worsens
- symptons persist for more than 7 days or clear up and occur again within a few days

Keep out of reach of children. If swallowed, get medical help or contact a Poison Control Center immediately

Directions:

Adults and children 2 years of age and older:

- use to clean minor cut, scrapes, and burns by thoroughly flushing the affected area
- let air dry
- cover with adhesive bandage or sterile gauze
- apply a small amount of this product on the area 1 to 3 times daily

Children under 2 years of age: do not use, consult a doctor

Inactive ingredients:

Aloe barbadensis Mill, Ethanol, Hydrastis canadensis L., Hydrogen Peroxide, Panax quinquefolis L., Water